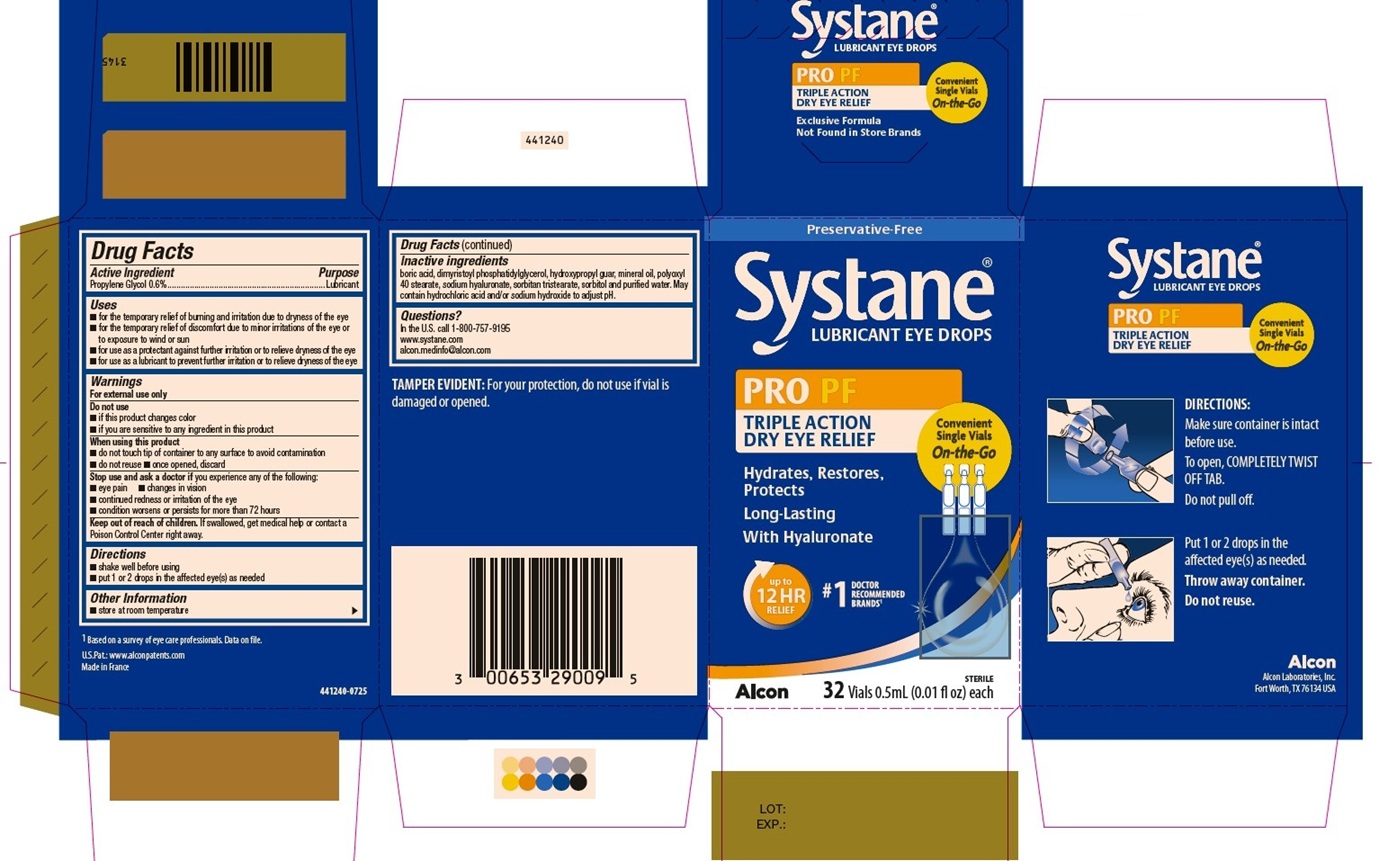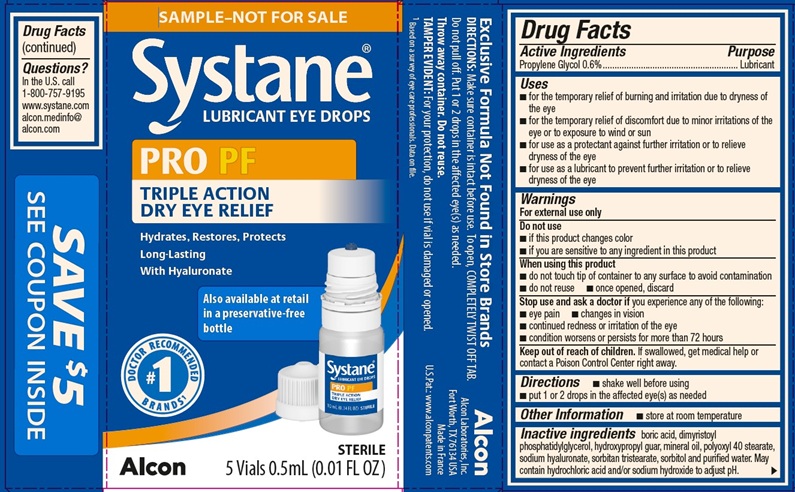 DRUG LABEL: Systane Pro PF
NDC: 0065-9308 | Form: EMULSION
Manufacturer: Alcon Laboratories, Inc.
Category: otc | Type: HUMAN OTC DRUG LABEL
Date: 20260114

ACTIVE INGREDIENTS: Propylene Glycol 6 mg/1 mL
INACTIVE INGREDIENTS: Boric Acid; Dimyristoylphosphatidylglycerol, Dl-; Guaraprolose (3500 Mpa.S At 1%); Mineral Oil; Polyoxyl 40 Stearate Type I; Hyaluronate Sodium; Sorbitan Tristearate; Sorbitol; Water; Hydrochloric Acid; Sodium Hydroxide

SYSTANE PRO PRESERVATIVE FREE
Drug Facts

ACTIVE INGREDIENT

Active Ingredients | Purpose
Propylene Glycol 0.6% | Lubricant

Uses

- for the temporary relief of burning and irritation due to dryness of the eye
- for the temporary relief of discomfort due to minor irritations of the eye or to exposure to wind or sun
- for use as a protectant against further irritation or to relieve dryness of the eye
- for use as a lubricant to prevent further irritation or to relieve dryness of the eye

Warnings

For external use only

Do not use

- if this product changes color
- if you are sensitive to any ingredient in this product

When using this product

- do not touch tip of container to any surface to avoid contamination
- do not reuse
- once opened, discard

Stop use and ask a doctor if you experience any of the following:

- eye pain
- changes in vision
- continued redness or irritation of the eye
- condition worsens or persists for more than 72 hours

Keep out of reach of children.

If swallowed, get medical help or contact a Poison Control Center right away.

Directions

- shake well before using
- put 1 or 2 drops in the affected eye(s) as needed

Other information

- store at room temperature

Inactive ingredients

boric acid, dimyristoyl phosphatidylglycerol, hydroxypropyl guar, mineral oil, polyoxyl 40 stearate, sodium hyaluronate, sorbitan tristearate, sorbitol and purified water. May contain hydrochloric acid and/or sodium hydroxide to adjust pH.

Questions?

In the U.S. call 1-800-757-9195
www.systane.com
alcon.medinfo@alcon.com

PRINCIPAL DISPLAY PANEL

Preservative-Free
Systane® LUBRICANT EYE DROPS
PRO PF
TRIPLE ACTION
DRY EYE RELIEF
Hydrates, Restores, Protects
Long-Lasting
With Hyaluronate
Convenient Single Vials On-the-Go
Up to 12 HR RELIEF
#1 DOCTOR RECOMMENDED BRANDS^1
Alcon
Sterile 32 Vials 0.5mL (0.01 fl oz) each
Side Panel:
Systane® LUBRICANT EYE DROPS
PRO PF
TRIPLE ACTION
DRY EYE RELIEF
Convenient Single Vials On-the-Go
Directions: Make sure container is intact before use. To open, COMPLETELY TWIST OFF
TAB.
Do not pull off. Put 1 or 2 drops in the affected eye(s) as needed.
Throw away container. Do not reuse.
TAMPER EVIDENT: For your protection, do not use if vial is damaged or opened.
Alcon
Alcon Laboratories, Inc.
Fort Worth, TX 76134 USA
^1Based on a survey of eye care professionals. Data on file.
U.S. Pat.: www.alconpatents.com
Made in France
441240-0725

Sample – Not for Sale
Systane® LUBRICANT EYE DROPS
PRO PF
TRIPLE ACTION
DRY EYE RELIEF
Hydrates, Restores, Protects
Long-Lasting
With Hyaluronate
Also available at retail in a preservative-free bottle
#1 DOCTOR RECOMMENDED BRANDS^1
Alcon
Sterile
5 Vials 0.5mL (0.01 FL OZ)
Side Panel:
Exclusive Formula Not Found in Store Brands
Directions: Make sure container is intact before use. To open, COMPLETELY TWIST OFF TAB.
Do not pull off. Put 1 or 2 drops in the affected eye(s) as needed.
Throw away container. Do not reuse.
TAMPER EVIDENT: For your protection, do not use if vial is damaged or opened.
^1Based on a survey of eye care professionals. Data on file.
Alcon
Alcon Laboratories, Inc.
Fort Worth, TX 76134 USA
Made in France
U.S. Pat.: www.alconpatents.com
440220